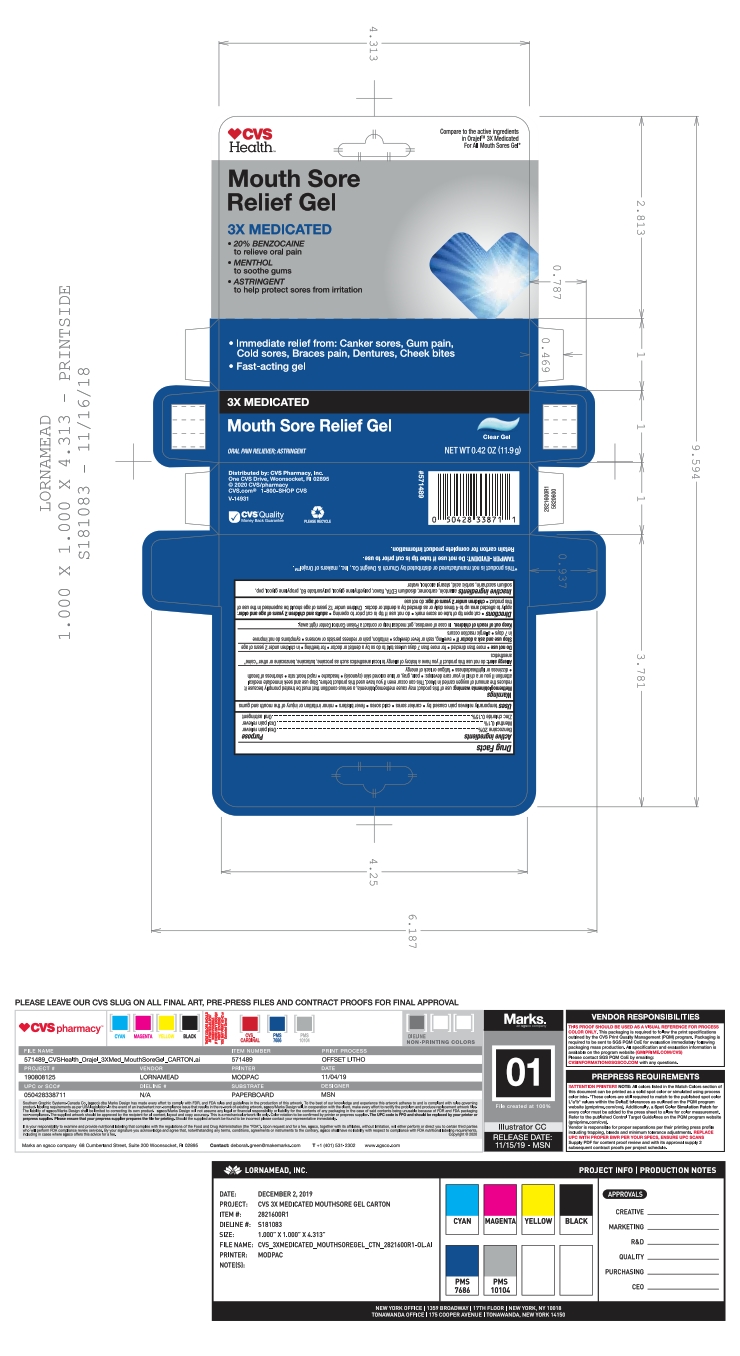 DRUG LABEL: 3x Medicated Mouth Sore Gel
NDC: 69842-660 | Form: GEL
Manufacturer: CVS
Category: otc | Type: HUMAN OTC DRUG LABEL
Date: 20251113

ACTIVE INGREDIENTS: BENZOCAINE 20 g/100 g; MENTHOL, UNSPECIFIED FORM 0.1 g/100 g; ZINC CHLORIDE 0.15 g/100 g
INACTIVE INGREDIENTS: POLYETHYLENE GLYCOL 400; CARBOMER HOMOPOLYMER TYPE B (ALLYL PENTAERYTHRITOL CROSSLINKED); PROPYLENE GLYCOL; POVIDONE K90; SORBIC ACID; STEARYL ALCOHOL; ALLANTOIN; WATER; EDETATE DISODIUM; POLYSORBATE 60; SACCHARIN SODIUM; METHYL SALICYLATE

5820600 3x Med Gel

ACTIVE INGREDIENT

Benzocaine 20% . . . Oral pain reliever

Menthol 0.1% . . . Oral pain reliever

Zinc chloride 0.15% . . . Oral astringent

PURPOSE

Uses

temporarily relives pain caused by * canker sores * cold sores * fever blisters * minor irritation or injury of the mouth and gums

WARNINGS

Methemoglobinemia warning: use of this product may cause methemoglobinemia, a serious condition that must be treated promptly because it reduces the amount of oxygen carried in blood. This can occur even if you have used this product before. Stop use and seek immediate medical attention if you or a child in your care develops: * pale, gray, or blue colored skin (cyanosis) * headache * rapid heart rate * shortness of breath * dizziness or lightheadedness * fatigue or lack of energy

Allergy alert: do not use this product if you have a history of allergy to local anesthetics such as procaine, butacaine, benzocaine or other "caine" anesthetics

Do not use * more than directed * for more than 7 days unless told to do so by a dentist or doctor * for teething * in children under 2 years of age

Stop use and ask a doctor if * swelling, rash or fever develops * irritation, pain or redness persists or worsens * symptoms do not improve in 7 days * allergic reaction occurs

Keep out of reach of children. In case of overdose, get medical help or contact a Poison Control Center right away.

Directions

cut open tip of tube on score mark * do not use if tip is cut prior to opening * adults and children 2 years of age and older: apply to affected area up to 4 times daily or as directed by a dentist or doctor. Children under 12 years of age shoul dbe supervised in the use of this product * children under 2 years of age: do not use

INACTIVE INGREDIENT

allantoin, carbomer, disodium EDTA, flavor, polyethylene glycol, polysorbate 60, propylene glycol, pvp, sodium saccharin, sorbic acid, stearyl alcohol, water